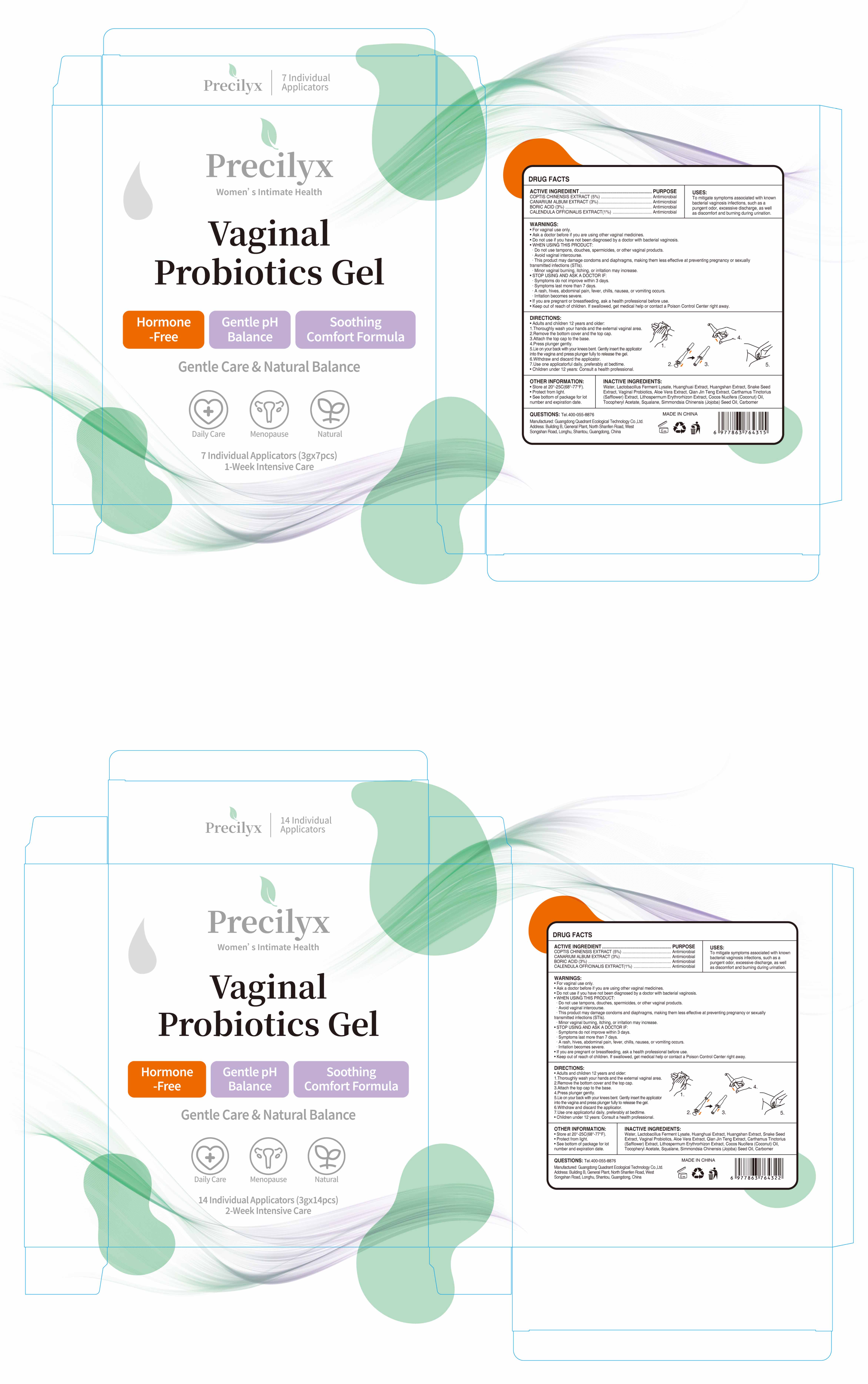 DRUG LABEL: Precilyx Vaginal Probiotics Gel
NDC: 76986-017 | Form: GEL
Manufacturer: Guangdong Quadrant Ecological Technology Co., Ltd.
Category: otc | Type: HUMAN OTC DRUG LABEL
Date: 20251222

ACTIVE INGREDIENTS: BORIC ACID 0.03 g/1 g; COPTIS CHINENSIS ROOT 0.05 g/1 g; CALENDULA OFFICINALIS FLOWER 0.01 g/1 g; CANARIUM ALBUM WHOLE 0.03 g/1 g
INACTIVE INGREDIENTS: ALOE VERA LEAF; LIMOSILACTOBACILLUS FERMENTUM; CARTHAMUS TINCTORIUS FLOWER BUD; CNIDIUM SEED; CARBOMER; COCOS NUCIFERA (COCONUT) OIL; STEPHANIA JAPONICA WHOLE; .ALPHA.-TOCOPHEROL ACETATE; SIMMONDSIA CHINENSIS (JOJOBA) SEED OIL; PSEUDOTSUGA MENZIESII WHOLE; WATER; SQUALANE; LITHOSPERMUM ERYTHRORHIZON ROOT

76986-017 Precilyx Vaginal Probiotics Gel

ACTIVE INGREDIENT

COPTIS CHINENSIS EXTRACT
CANARIUM ALBUM EXTRACT
BORIC ACID
CALENDULA OFFICINALIS EXTRACT

PURPOSE

Antimicrobial

INDICATIONS AND USAGE

To mitigate symptoms associated with knownbacterial vaginosis infections, such as apungent odor, excessive discharge, as wel!as discomfort and burning during urination.

WARNINGS

For vaginal use only.

Do not use if you have not been diagnosed by a doctor with bacterial vaginosis.

Do not use tampons, douches, spermicides, or other vaginal products.
Avoid vaginal intercourse.
This product may damage condoms and diaphragms, making them less effective at preventing pregnancy or sexually transmitted infections (STls)
Minor vaginal buring, itching, or irritation may increase.

STOP USE

Symptoms do not improve within 3 days.
Symptoms last more than 7 days.
A rash, hives, abdominal pain, fever, chills, nausea, or vomiting occurslrritation becomes severe.

Keep out of reach of children. lf swallowed, get medical help or contact a Poison Control Center right away.

DOSAGE AND ADMINISTRATION

Adults and children 12 years and older:
1.Thoroughly wash your hands and the external vaginal area.
2.Remove the bottom cover and the top cap.
3.Attach the top cap to the base.
4.Press plunger gently.
5.Lie on your back with your knees bent Gently insert the applicatorinto the vagina and press plunger fully to release the gel.
6.Withdraw and discard the applicator.
7.Use one applicatorful daily, preferably at bedtime
Children under 12 years: Consult a health professional.

INACTIVE INGREDIENT

Water, Lactobacillus Ferment Lysate, Huanghuai Extract, Huangshan Extract, Snake SeedExtract, Vaginal Probiotics, Aloe Vera Extract, Qian Jin Teng Extract, Carthamus Tinctorius(Safflower) Extract, Lithospermum Ervthrorhizon Extract, Cocos Nucifera (Coconut) Oil.Tocopheryl Acetate,Squalane, Simmondsia Chinensis (Jojoba) Seed Oil. Carbomer